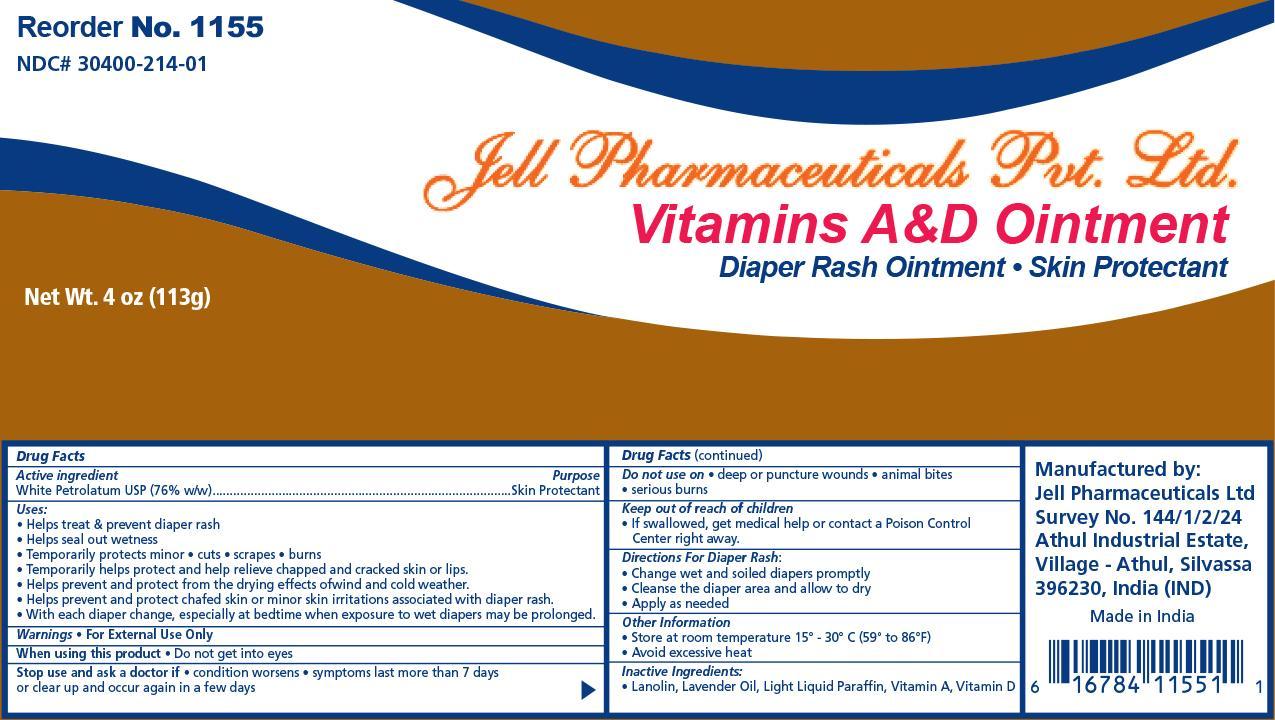 DRUG LABEL: Jell Pharmaceuticals Vitamin A D
NDC: 30400-214 | Form: OINTMENT
Manufacturer: Jell Pharmaceuticals Pvt. Ltd.
Category: otc | Type: HUMAN OTC DRUG LABEL
Date: 20241217

ACTIVE INGREDIENTS: PETROLATUM 0.76 g/1 g
INACTIVE INGREDIENTS: VITAMIN A PALMITATE; LANOLIN; LIGHT MINERAL OIL; CHOLECALCIFEROL

Vitamin A D

Active Ingredient Purpose

White Petrolatum USP (76%) Skin Protectant

Purpose:

- Helps treat and prevent diaper rash
- Helps seal out wetness

- Temporarily protects minor * cuts * scrapes * burns
- Temporarily helps protect and help relieve chapped and cracked skin and lips
- Helps prevent and protect from the drying effects of wind and cold weather
- Helps prevent and protect chafed skin or minor skin irritations associated with diaper rash
- With each diaper change, especially at bedtime when exposure to wet diapers may be prolonged

Warnings:

For External Use Only

When using this product:

- Do not get in eyes

Dosage & Administration

Stop use and ask a doctor if:

- If condition worsens
- symptoms last more than 7 days or clear up and occur again in a few days

Do not use:

- Deep or puncture wounds
- animal bites
- serious burns

Keep out of reach of children

- If swallowed, get medical help or contact a Poison Control Center right away.

Indications & Usage

Directions for diaper rash:

- Change wet and soiled diapers promptly
- Cleanse the diaper area and allow to dry
- Apply as needed

Other information:

- Store at room temperature 15 deg C to 30 deg C 59 deg F to 86 deg F
- Avoid excessive heat

Inactive Ingredients:

Inactive Ingredients: Light Liquid Parafin, Vitamin A, Vitamin D

Principal Display Panel

Jell Vit AD.jpg